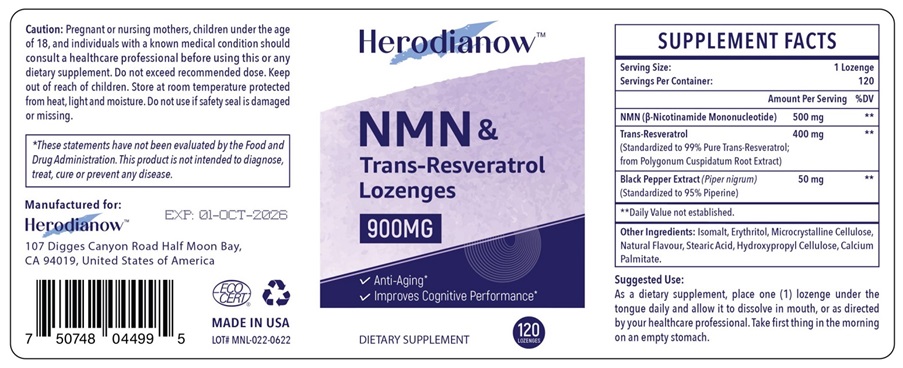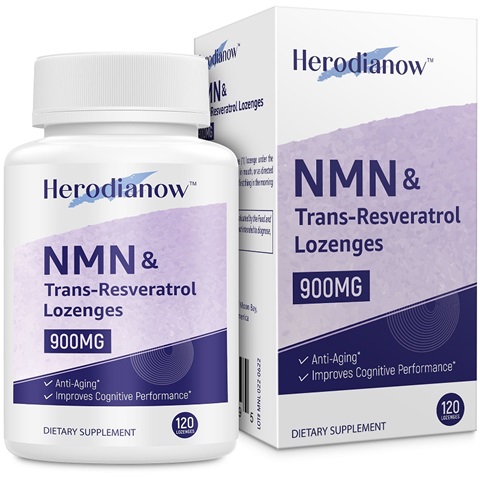 DRUG LABEL: Herodianow
NDC: 83459-003 | Form: LOZENGE
Manufacturer: HEALGROW INC
Category: otc | Type: HUMAN OTC DRUG LABEL
Date: 20231026

ACTIVE INGREDIENTS: NICOTINAMIDE MONONUCLEOTIDE 500 mg/1 1; RESVERATROL 400 mg/1 1; WHITE PEPPER 50 mg/1 1
INACTIVE INGREDIENTS: ISOMALT; ERYTHRITOL; MICROCRYSTALLINE CELLULOSE; STEARIC ACID; HYDROXYPROPYL CELLULOSE, UNSPECIFIED; CALCIUM PALMITATE

Active Ingredient

β-Nicotinamide Mononucleotide 500mg

Resveratrol 400mg

Black Pepper Extract 50mg

Waring

Pregnant or nursing mothers, children under the age of 18 and individuals with a known medical conditions should consult a healthcare professional before using this or any dietary supplement. Do not exceed recommended dosage. keep out of reach of children.

Direction

As a dietary supplement, place one lozenge under the tongue daily and allow it to dissolve in mouth, or as direacted by your healthcare professional. Take first thing in the morning on an empty stomach

Other information

Store at room temperature protected from heat, light and moisture. Do not use if safety seal is damaged or missing.